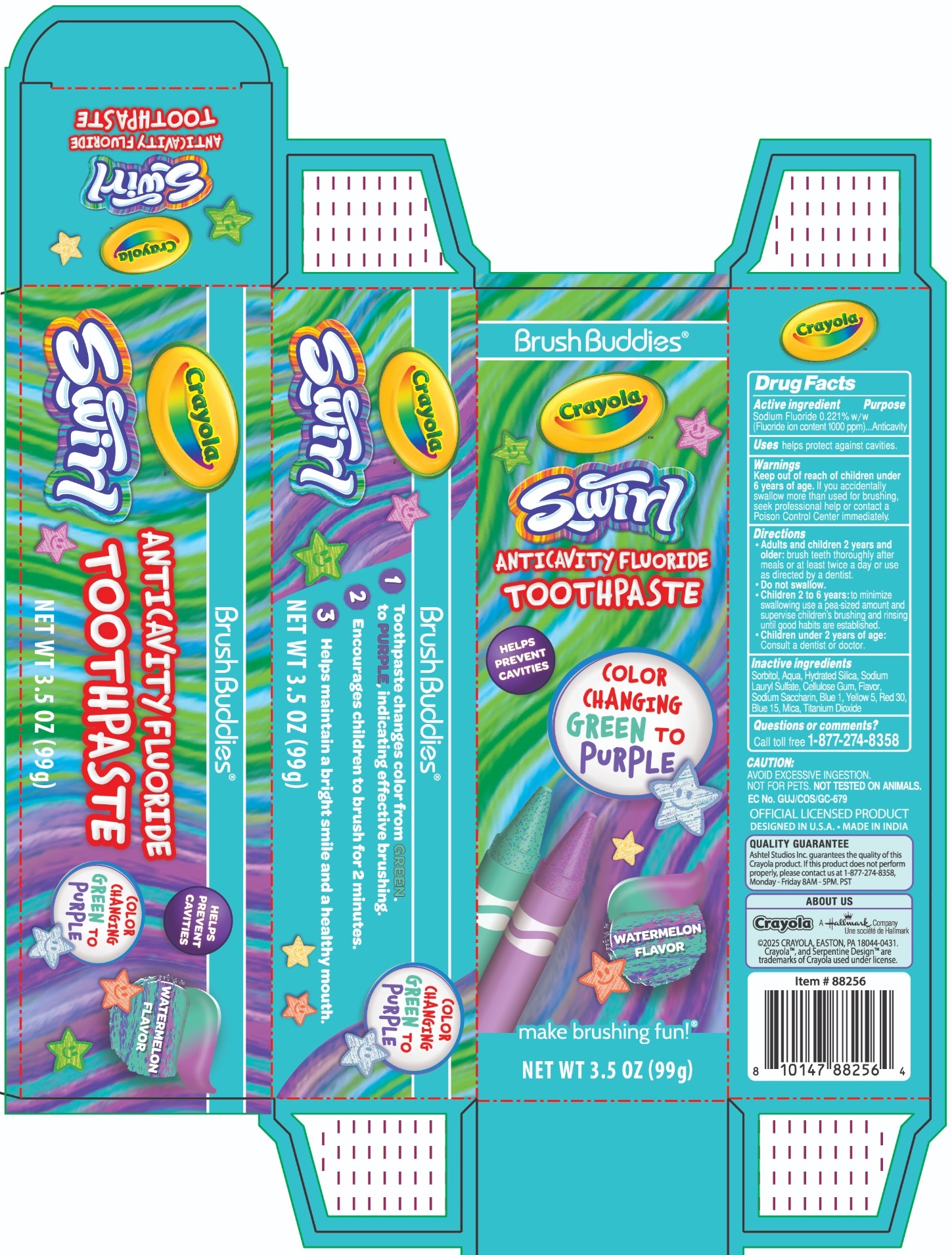 DRUG LABEL: Brush Buddies Crayola Swirl ANTICAVITY FLUORIDE WATERMELON FLAVOR
NDC: 70108-108 | Form: PASTE, DENTIFRICE
Manufacturer: Ashtel Studios, Inc.
Category: otc | Type: HUMAN OTC DRUG LABEL
Date: 20241225

ACTIVE INGREDIENTS: SODIUM FLUORIDE 0.221 g/100 g
INACTIVE INGREDIENTS: SORBITOL; WATER; HYDRATED SILICA; SODIUM LAURYL SULFATE; CARBOXYMETHYLCELLULOSE SODIUM, UNSPECIFIED; SACCHARIN SODIUM; FD&C BLUE NO. 1; FD&C YELLOW NO. 5; D&C RED NO. 30; PHTHALOCYANINE BLUE; MICA; TITANIUM DIOXIDE

Brush Buddies® Crayola Swirl ANTICAVITY FLUORIDE TOOTHPASTE - WATERMELON FLAVOR

Active ingredient

Sodium Fluoride 0.221% w/w
(Fluoride ion content 1000 ppm)

Purpose

Anticavity

Uses

helps protect against cavities.

Warnings

Keep out of reach of children under 6 years of age. If you accidentally swallow more than used for brushing, seek professional help or contact a Poison Control Center immediately.

Directions

• Adults and children 2 years and older: brush teeth thoroughly after meals or at least twice a day or use as directed by a dentist.

• Do not swallow.

• Children 2 to 6 years: to minimize swallowing use a pea-sized amount and supervise children's brushing and rinsing until good habits are established.

• Children under 2 years of age: Consult a dentist or doctor.

Inactive ingredients

Sorbitol, Aqua, Hydrated Silica, Sodium Lauryl Sulfate, Cellulose Gum, Flavor, Sodium Saccharin, Blue 1, Yellow 5, Red 30, Blue 15, Mica, Titanium Dioxide

Questions or comments?

Call toll free 1-877-274-8358

HELPS PREVENT CAVITIES

COLOR CHANGING GREEN TO PURPLE

make brushing fun!®

CAUTION:
AVOID EXCESSIVE INGESTION.
NOT FOR PETS. NOT TESTED ON ANIMALS.

EC No. GUJ/COS/GC-679
OFFICIAL LICENSED PRODUCT
DESIGNED IN U.S.A. • MADE IN INDIA

QUALITY GUARANTEE
Ashtel Studios Inc. guarantees the quality of this Crayola product. If this product does not perform properly, please contact us at 1-877-274-8358, Monday - Friday 8AM - 5PM. PST

ABOUT US
Crayola A Hallmark Company
©2025 CRAYOLA, EASTON, PA 18044-0431.
Crayola™, and Serpentine Design™ are trademarks of Crayola used under license.

1. Toothpaste changes color from GREEN. to PURPLE, indicating effective brushing.
2. Encourages children to brush for 2 minutes.
3. Helps maintain a bright smile and a healthy mouth.